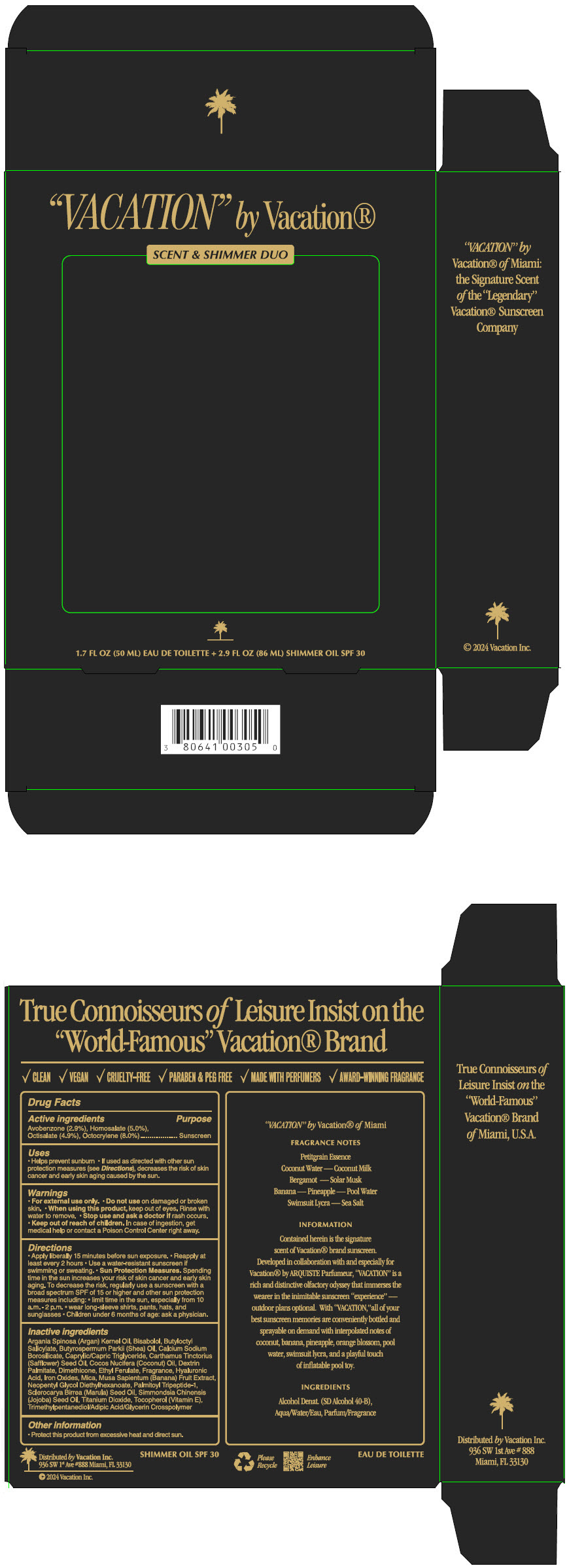 DRUG LABEL: Vacation by Vacation Scent and Shimmer Duo
NDC: 80641-203 | Form: KIT | Route: TOPICAL
Manufacturer: Vacation Inc.
Category: otc | Type: HUMAN OTC DRUG LABEL
Date: 20240528

ACTIVE INGREDIENTS: Avobenzone 2.9 g/100 mL; Homosalate 5 g/100 mL; Octisalate 4.9 g/100 mL; Octocrylene 8 g/100 mL
INACTIVE INGREDIENTS: ARGAN OIL; LEVOMENOL; BUTYLOCTYL SALICYLATE; SHEANUT OIL; MEDIUM-CHAIN TRIGLYCERIDES; SAFFLOWER OIL; COCONUT OIL; DIMETHICONE; ETHYL FERULATE; HYALURONIC ACID; FERRIC OXIDE RED; MICA; BANANA; NEOPENTYL GLYCOL DIETHYLHEXANOATE; PALMITOYL TRIPEPTIDE-1; SCLEROCARYA BIRREA SEED OIL; JOJOBA OIL; TITANIUM DIOXIDE; .ALPHA.-TOCOPHEROL

Vacation by Vacation® Scent & Shimmer Duo

Drug Facts

Active ingredients

Avobenzone (2.9%), Homosalate (5.0%), Octisalate (4.9%), Octocrylene (8.0%)

Purpose

Sunscreen

Uses

- Helps prevent sunburn
- If used as directed with other sun protection measures (see Directions), decreases the risk of skin cancer and early skin aging caused by the sun.

Warnings

- For external use only.

- Do not use on damaged or broken skin.

- When using this product, keep out of eyes. Rinse with water to remove.

- Stop use and ask a doctor if rash occurs.

- Keep out of reach of children. In case of ingestion, get medical help or contact a Poison Control Center right away.

Directions

- Apply liberally 15 minutes before sun exposure.
- Reapply at least every 2 hours
- Use a water-resistant sunscreen if swimming or sweating.
- Sun Protection Measures. Spending time in the sun increases your risk of skin cancer and early skin aging. To decrease the risk, regularly use a sunscreen with a broad spectrum SPF of 15 or higher and other sun protection measures including:
  - limit time in the sun, especially from 10 a.m.-2 p.m.
  - wear long-sleeve shirts, pants, hats and sunglasses
- Children under 6 months of age: ask a physician.

Inactive ingredients

Argania Spinosa (Argan) Kernel Oil, Bisabolol, Butyloctyl Salicylate, Butyrospermum Parkii (Shea) Oil, Calcium Sodium Borosilicate, Caprylic/Capric Triglyceride, Carthamus Tinctorius (Safflower) Seed Oil, Cocos Nucifera (Coconut) Oil, Dextrin Palmitate, Dimethicone, Ethyl Ferulate, Fragrance, Hyaluronic Acid, Iron Oxides, Mica, Musa Sapientum (Banana) Fruit Extract, Neopentyl Glycol Diethylhexanoate, Palmitoyl Tripeptide-1, Sclerocarya Birrea (Marula) Seed Oil, Simmondsia Chinensis (Jojoba) Seed Oil, Titanium Dioxide, Tocopherol (Vitamin E), Trimethylpentanediol/Adipic Acid/Glycerin Crosspolymer

Other information

- Protect this product from excessive heat and direct sun.

Distributed by Vacation Inc.
936 SW 1st Ave #888 Miami, FL 33130

PRINCIPAL DISPLAY PANEL - Kit Carton

"VACATION" by Vacation®

SCENT & SHIMMER DUO

1.7 FL OZ (50 ML) EAU DE TOILETTE + 2.9 FL OZ (86 ML) SHIMMER OIL SPF 30